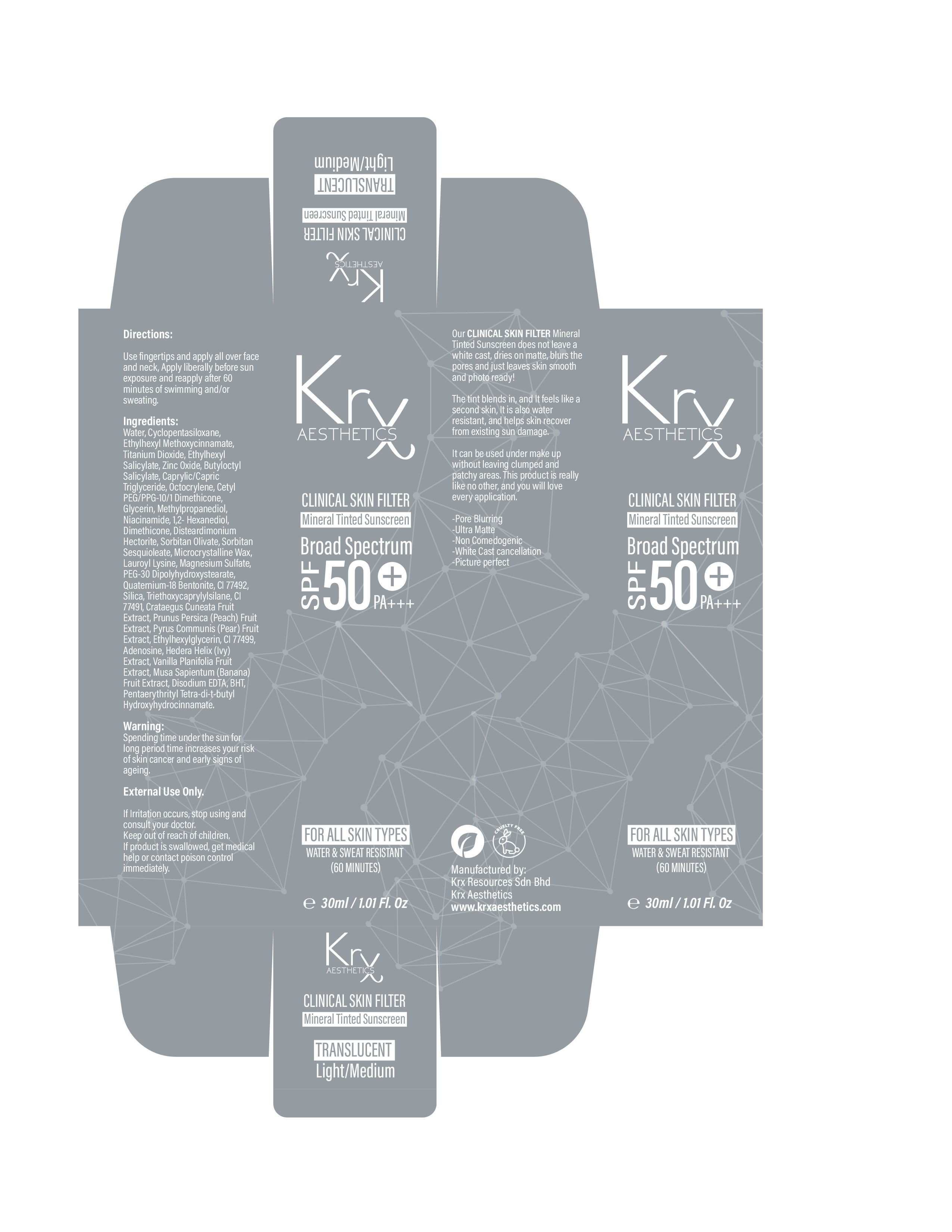 DRUG LABEL: Clinical Skin Filter Tinted Sunscreen
NDC: 84755-0003 | Form: CREAM
Manufacturer: KRX RESOURCES SDN. BHD.
Category: otc | Type: HUMAN OTC DRUG LABEL
Date: 20251018

ACTIVE INGREDIENTS: ZINC OXIDE 1.182 mg/30 mL; TITANIUM DIOXIDE 1.734 mg/30 mL; OCTOCRYLENE 0.9 mg/30 mL
INACTIVE INGREDIENTS: LAUROYL LYSINE; ETHYLHEXYL METHOXYCRYLENE; METHYLPROPANEDIOL; NIACINAMIDE; PENTAMETHYL CYCLOPENTASILOXANE; BUTYLOCTYL SALICYLATE; SORBITAN OLIVATE; MAGNESIUM DISODIUM EDTA; HEDERA HELIX LEAF; CETYL PEG/PPG-10/1 DIMETHICONE (HLB 2); CRATAEGUS CUNEATA FRUIT; DISTEARDIMONIUM HECTORITE; TRIETHOXYCAPRYLYLSILANE; DIMETHICONE 100; QUATERNIUM-18; PYRUS COMMUNIS WHOLE; SORBITAN SESQUIOLEATE; POTASSIUM MAGNESIUM SULFATE; PEG-30 DIPOLYHYDROXYSTEARATE; GLYCERIN; PRUNUS PERSICA FRUITING TOP; ETHYLHEXYLGLYCERIN; VANILLA PLANIFOLIA WHOLE; WATER; 1,2-HEXANEDIOL; MICROCRYSTALLINE WAX

DOSAGE AND ADMINISTRATION

Use fingertips and apply all over face and neck, Apply liberally before sun exposure and reapply after 60 minutes of swimming and/or sweating.

Warning:
Spending time under the sun for
long period time increases your risk of skin cancer and early signs of ageing.
External Use Only.
If Irritation occurs, stop using and
consult your doctor.
Keep out of reach of children.
If product is swallowed, get medical help or contact poison control immediately.

Inactive Ingredients:
Water, Cyclopentasiloxane, Ethylhexyl Methoxycinnamate, Titanium Dioxide, Ethylhexyl Salicylate, Zinc Oxide, Butyloctyl Salicylate, Caprylic/Capric Triglyceride, Octocrylene, Cetyl PEG/PPG-10/1 Dimethicone,
Glycerin, Methylpropanediol, Niacinamide, 1,2- Hexanediol, Dimethicone, Disteardimonium Hectorite, Sorbitan Olivate, Sorbitan Sesquioleate, Microcrystalline Wax, Lauroyl Lysine, Magnesium Sulfate, PEG-30 Dipolyhydroxystearate, Quaternium-18 Bentonite, CI 77492, Silica, Triethoxycaprylylsilane, CI 77491, Crataegus Cuneata Fruit Extract, Prunus Persica (Peach) Fruit Extract, Pyrus Communis (Pear) Fruit Extract, Ethylhexylglycerin, CI 77499, Adenosine, Hedera Helix (Ivy) Extract, Vanilla Planifolia Fruit Extract, Musa Sapientum (Banana) Fruit Extract, Disodium EDTA, BHT, Pentaerythrityl Tetra-di-t-butyl Hydroxyhydrocinnamate.

INDICATIONS AND USAGE

Our CLINICAL SKIN FILTER Mineral Tinted Sunscreen does not leave a white cast, dries on matte, blurs the pores and just leaves skin smooth and photo ready!
The tint blends in, and It feels like a second skin, It is also water resistant, and helps skin recover from existing sun damage.
It can be used under make up without leaving clumped and patchy areas. This product is really like no other, and you will love every application.
-Pore Blurring -Ultra Matte
-Non Comedogenic
-White Cast cancellation -Picture perfect
CRUELTY FREE.

Keep out of reach of children.

PURPOSE

FOR ALL SKIN TYPES WATER & SWEAT RESISTANT (60 MINUTES)

CLINICAL SKIN FILTER Mineral Tinted Sunscreen
TRANSLUCENT Light/Medium

Directions:
Use fingertips and apply all over face and neck, Apply liberally before sun exposure and reapply after 60
minutes of swimming and/or sweating.

Active:
Cyclopentasiloxane -8%
Titanium Dioxide - 5.78%
Zinc Oxide - 3.94%
Octocrylene -3%

PACKAGE LABEL

CLINICAL SKIN FILTER Mineral Tinted Sunscreen TRANSLUCENT Light/Medium